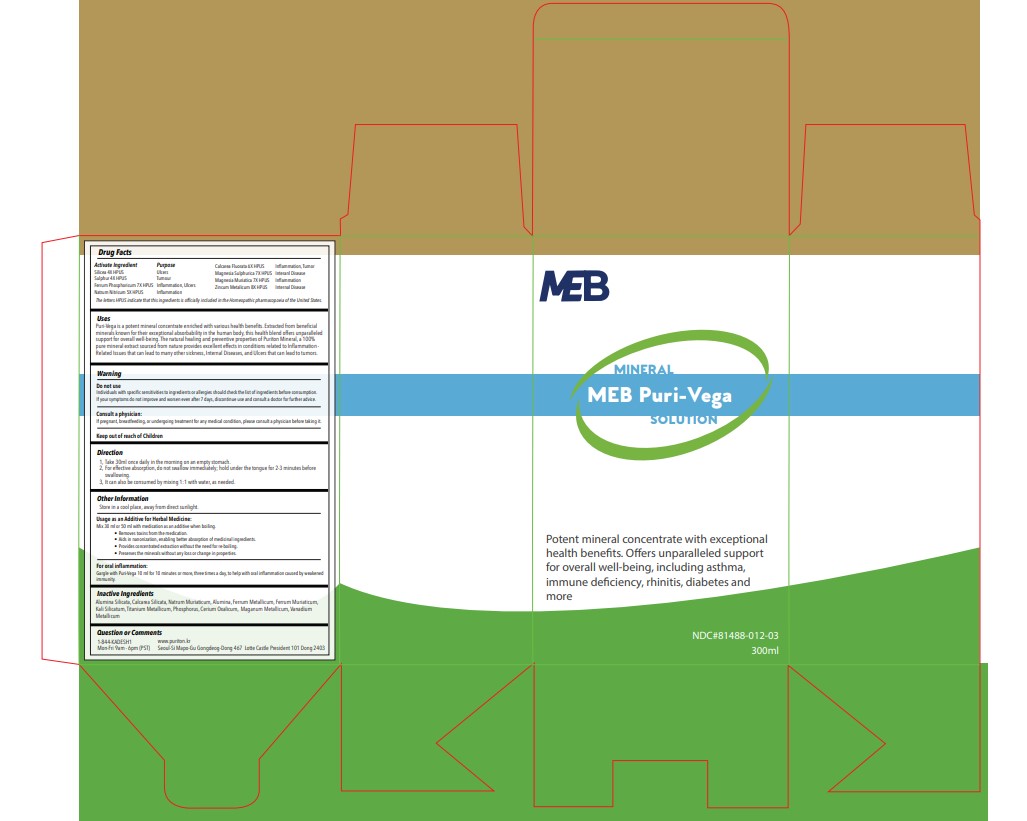 DRUG LABEL: MEB Puri-vega
NDC: 81488-013 | Form: LIQUID
Manufacturer: Kadesh Incoporation Co,Ltd
Category: homeopathic | Type: HUMAN OTC DRUG LABEL
Date: 20230905

ACTIVE INGREDIENTS: CALCIUM FLUORIDE 6 [hp_X]/300 mL; MAGNESIUM SULFATE HEPTAHYDRATE 7 [hp_X]/300 mL; SODIUM NITRATE 5 [hp_X]/300 mL; ZINC 8 [hp_X]/300 mL; FERROSOFERRIC PHOSPHATE 7 [hp_X]/300 mL; MAGNESIUM CHLORIDE 7 [hp_X]/300 mL; SILICON DIOXIDE 4 [hp_X]/300 mL; SULFUR 4 [hp_X]/300 mL
INACTIVE INGREDIENTS: FERRIC CHLORIDE HEXAHYDRATE; POTASSIUM SILICATE; CEROUS OXALATE NONAHYDRATE; MANGANESE; VANADIUM; CALCIUM SILICATE; ALUMINUM OXIDE; IRON; SODIUM CHLORIDE; TITANIUM; PHOSPHORUS; KAOLIN

ACTIVE INGREDIENT

Sulphur, Ferrum Phosphoricum, Natrum Nitricum, Calcarea Fluorata, Magnesia Sulphurica, Magnesia Muriatica, Zincum Metalicum

INACTIVE INGREDIENT

Alumina Silicata, Calcarea Silicata, Natrum Muriaticum, Alumina, Ferrum Metallicum, Ferrum Muriaticum, Kali Silicatum, Titanium Metallicum, Phosphorus, Cerium Oxalicum, Maganum Metallicum, Vanadium Metallicum

Active Ingredients Purpose

Silicea 4X HPUS ………………………………….. Ulcers

Sulphur 4X HPUS………………………………….. Tumour

Ferrum Phosphoricum 7X HPUS.………………… Inflammation, Ulcers

Natrum Nitricum 5X HPUS……………………….. Inflammation

Calcarea Fluorata 6X HPUS……………………… Inflammation, Tumor

Magnesia Sulphurica 7X HPUS …………………. Internal Disease

Magnesia Muriatica 7X HPUS…………………. Inflammation

Zincum Metalicum 8X …………………………….. Internal Disease

INDICATIONS AND USAGE

MEB Puri-Vega is potent mineral concentrate with exceptional health benefits. Offers unparalleled support for overall well-being, including asthma, immune deficiency, rhinitis, diabetes and more.”

Usage:

Puri-Vega is a potent mineral concentrate enriched with various health benefits. Extracted from beneficial minerals known for their exceptional absorbability in the human body, this health blend offers unparalleled support for overall well-being. The natural healing and preventive properties of Puriton Mineral, a 100% pure mineral extract sourced from nature provides excellent effects in conditions related to Inflammation-Related Issues that can lead to many other sickness, Internal Diseases, and Ulcers that can lead to tumors.

DOSAGE AND ADMINISTRATION

Direction

Take 30ml once daily in the morning on an empty stomach.

For effective absorption, do not swallow immediately; hold under the tongue for 2-3 minutes before swallowing.

It can also be consumed by mixing 1:1 with water, as needed.

Usage as an Additive for Herbal Medicine:

Mix 30 ml or 50 ml with medication as an additive when boiling.

Removes toxins from the medication.

Aids in nanonization, enabling better absorption of medicinal ingredients.

Provides concentrated extraction without the need for re-boiling.

Preserves the minerals without any loss or change in properties.

For oral inflammation:

Gargle with Puri-Vega 10 ml for 10 minutes or more, three times a day, to help with oral inflammation caused by weakened immunity.

WARNINGS

Individuals with specific sensitivities to ingredients or allergies should check the list of ingredients before consumption.

If your symptoms do not improve and worsen even after 7 days, discontinue use and consult a doctor for further advice.

ASK DOCTOR

If pregnant, breastfeeding, or undergoing treatment for any medical condition, please consult a physician before taking it.

RECENT MAJOR CHANGES

Typo fixed in Indication and Usage

PACKAGE LABEL

MEB Vega-Puri. NDC: 81488-013-03